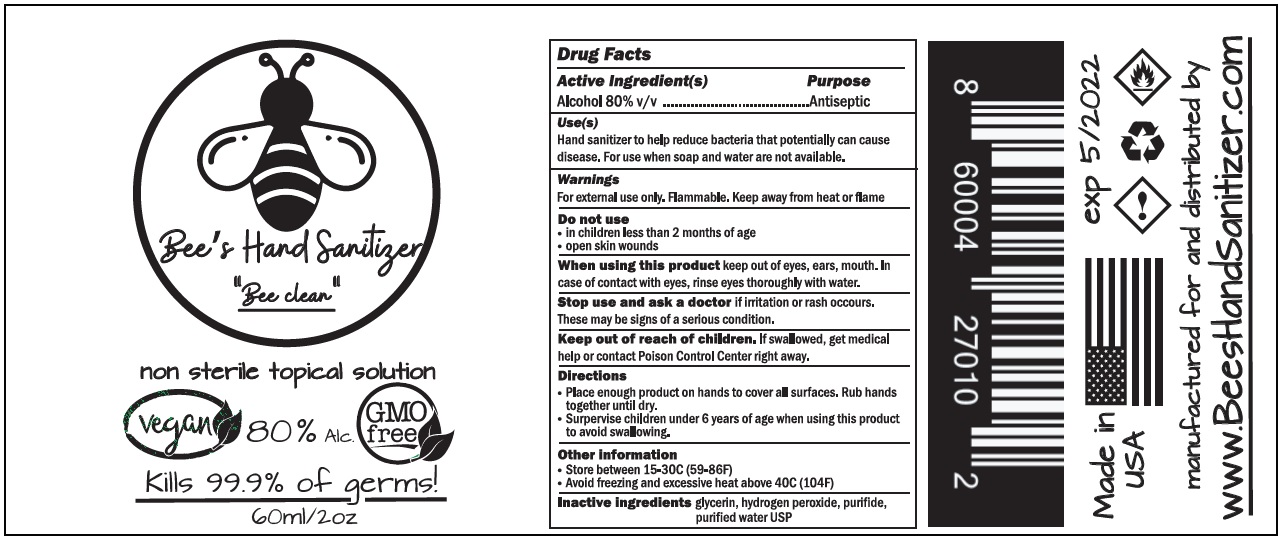 DRUG LABEL: Bees Hand Sanitizer
NDC: 79169-001 | Form: SOLUTION
Manufacturer: Bees Hand Sanitizer, Inc.
Category: otc | Type: HUMAN OTC DRUG LABEL
Date: 20200720

ACTIVE INGREDIENTS: ALCOHOL 80 mL/100 mL
INACTIVE INGREDIENTS: GLYCERIN; HYDROGEN PEROXIDE; WATER

Bees's Hand Sanitizer

Active Ingredient(s)

Alcohol 80% v/v

Purpose

Antiseptic

Uses(s)

Hand sanitizer to help reduce bacteria that potentially can cause disease. For use when soap and water are not available.

Warnings

For external use only. Flammable. Keep away from heat or flame

Do not use

•In children less than 2 months of age

• open skin wounds

When using this product keep out of eyes, ears, mouth. In case of contact with eyes, rinse eyes thoroughly with water.

Stop use and ask a doctor if irritation or rash occurs. These may be signs of a serious condition.

Keep out if reach of children.

If swallowed, get medical help or contact Poison Control Center right away.

Directions

• Place enough product on hands to cover all surfaces. Rub hands together until dry.

• Supervise children under 6 years of age when using this product to avoid swallowing.

Other information

• Store between 15-30C (59-86F)

• Avoid freezing and excessive heat above 40C (104F)

Inactive ingredients

glycerin, hydrogen peroxide, purified water USP

"Bee clean"

non sterile topical solution

Vegan

80% Alc.

GMO free

Kills 99.9% of germs!

Made in uSA

manufactured for and distributed by

www.BeesHandSanitizer.com

exp 5/2022